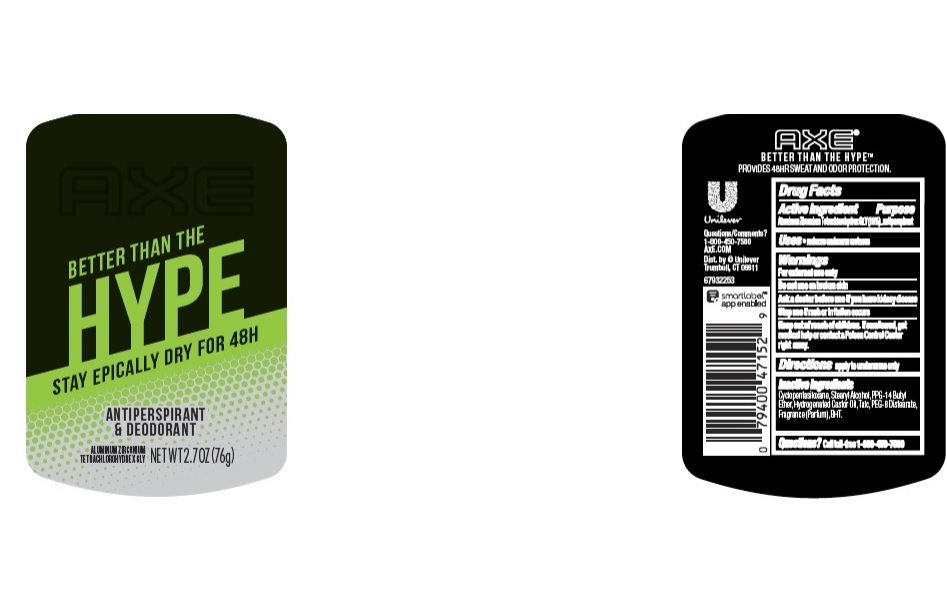 DRUG LABEL: Axe
NDC: 64942-1665 | Form: STICK
Manufacturer: Conopco Inc. d/b/a/ Unilever
Category: otc | Type: HUMAN OTC DRUG LABEL
Date: 20221207

ACTIVE INGREDIENTS: ALUMINUM ZIRCONIUM TETRACHLOROHYDREX GLY 19 g/100 g
INACTIVE INGREDIENTS: PEG-8 DISTEARATE; TALC; CYCLOMETHICONE 5; HYDROGENATED CASTOR OIL; BUTYLATED HYDROXYTOLUENE; PPG-14 BUTYL ETHER; STEARYL ALCOHOL

Axe Better Than The Hype Antiperspirant and Deodorant

AXE BETTER THAN THE HYPE ANTIPERSPIRANT AND DEODORANT - aluminum zirconium tetrachlorohydrex gly stick

Axe Better Than The Hype Antiperspirant and Deodorant

Drug Facts

Active ingredient

Aluminum Zirconium Tetrachlorohydrex GLY (19.0 %)

Purpose

antiperspirant

Uses

• reduces underarm wetness

Warnings

• For external use only.
• Do not use on broken skin .
• Ask a doctor before use if you have kidney disease.
• Stop use if rash or irritation occurs.

• Keep out of reach of children.

If swallowed, get medical help or contact a Poison Control Center right away.

Directions

apply to underarms only

Inactive ingredients

Cyclopentasiloxane, Stearyl Alcohol, PPG-14 Butyl Ether, Hydrogenated Castor Oil, Talc, PEG-8 Distearate, Fragrance (Parfum), BHT.

Questions?

Call toll-free 1-800-450-7580